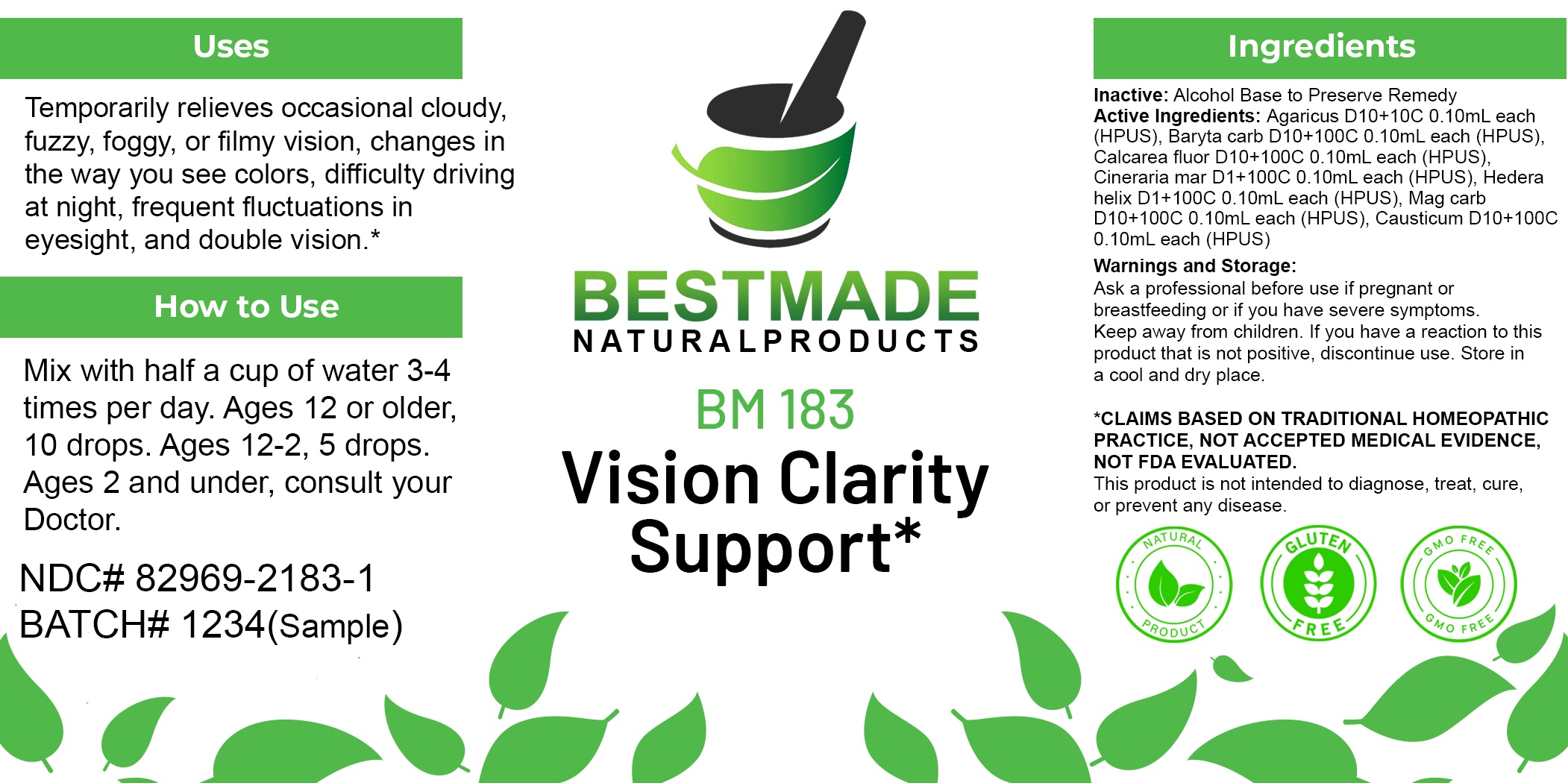 DRUG LABEL: Bestmade Natural Products BM183
NDC: 82969-2183 | Form: LIQUID
Manufacturer: Bestmade Natural Products
Category: homeopathic | Type: HUMAN OTC DRUG LABEL
Date: 20250219

ACTIVE INGREDIENTS: JACOBAEA MARITIMA WHOLE 30 [hp_C]/30 [hp_C]; CAUSTICUM 30 [hp_C]/30 [hp_C]; AMANITA MUSCARIA FRUITING BODY 30 [hp_C]/30 [hp_C]; MAGNESIUM CARBONATE 30 [hp_C]/30 [hp_C]; BARIUM CARBONATE 30 [hp_C]/30 [hp_C]; CALCIUM FLUORIDE 30 [hp_C]/30 [hp_C]; HEDERA HELIX FLOWERING TWIG 30 [hp_C]/30 [hp_C]
INACTIVE INGREDIENTS: ALCOHOL 30 [hp_C]/30 [hp_C]

BM183

DOSAGE AND ADMINISTRATION

How to Use

Mix with half a cup of water 3-4 times per day. Ages 12 or older, 10 drops. Ages 12-2, 5 drops. Ages 2 and under, consult your Doctor.

Inactive:

Alcohol Base to Preserve Product

ACTIVE INGREDIENTS
Agaricus D10+10C 0.10mL each (HPUS), Baryta carb D10+100C 0.10mL each (HPUS), Calcarea fluor D10+100C 0.10mL each (HPUS), Cineraria mar D1+100C 0.10mL each (HPUS), Hedera helix D1+100C 0.10mL each (HPUS), Mag carb D10+100C 0.10mL each (HPUS), Causticum D10+100C 0.10mL each (HPUS)

Uses
Temporarily relieves occasional cloudy, fuzzy, foggy, or filmy vision, changes in the way you see colors, difficulty driving at night, frequent fluctuations in eyesight, and double vision.*

Uses
Temporarily relieves occasional cloudy, fuzzy, foggy, or filmy vision, changes in the way you see colors, difficulty driving at night, frequent fluctuations in eyesight, and double vision.*

KEEP OUT OF REACH OF CHILDREN

Warnings and Storage:

Ask a professional before use if pregnant or breastfeeding or if you have severe symptoms.

Keep away from children. If you have a reaction to this product that is not positive, discontinue use. Store in a cool and dry place

*CLAIMS BASED ON TRADITIONAL HOMEOPATHIC PRACTICE, NOT ACCEPTED MEDICAL EVIDENCE NOT FDA EVALUATED.
This product is not intended to diagnose, treat, cure, or prevent any disease.

Warnings and Storage:

Ask a professional before use if pregnant or breastfeeding or if you have severe symptoms.

Keep away from children. If you have a reaction to this product that is not positive, discontinue use. Store in a cool and dry place

*CLAIMS BASED ON TRADITIONAL HOMEOPATHIC PRACTICE, NOT ACCEPTED MEDICAL EVIDENCE NOT FDA EVALUATED.
This product is not intended to diagnose, treat, cure, or prevent any disease.

Entire package label